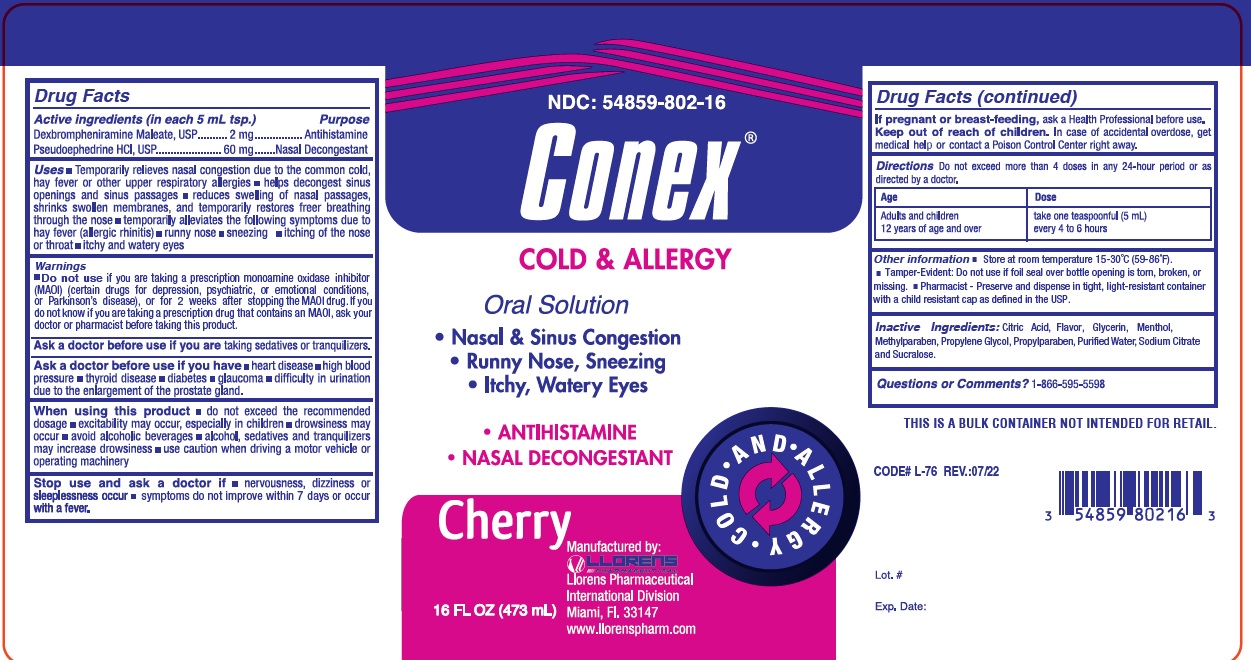 DRUG LABEL: Conex
NDC: 54859-802 | Form: LIQUID
Manufacturer: Llorens Pharmaceutical International Division
Category: otc | Type: HUMAN OTC DRUG LABEL
Date: 20241227

ACTIVE INGREDIENTS: DEXBROMPHENIRAMINE MALEATE 1 mg/5 mL; PSEUDOEPHEDRINE HYDROCHLORIDE 30 mg/5 mL
INACTIVE INGREDIENTS: SODIUM CITRATE; WATER; SUCRALOSE; CITRIC ACID MONOHYDRATE; GLYCERIN; MENTHOL; METHYLPARABEN; PROPYLENE GLYCOL; PROPYLPARABEN

Llorens-ConexLiq 802

Active Ingredients (in each 5 mL tsp.)

Dexbrompheniramine Maleate, USP .......... 1 mg .................... Antihistamine

Pseudoephedrine HCL, USP ............ 30 mg ...................... Nasal Decongestant

Uses:

- Temporarily relieves nasal congestion due to common cold, hay fever or other upper respiratory allergies
- Helps decongest sinus openings and sinus passages
- Reduces swelling of nasal passages, shrinks swollen membranes, and temporarily restores freer breathing through the nose
- Temporarily alleviates the following symtoms due to hay fever (allergic rhinitis) : runny nose, sneezing, itching of the nose or throat, itchy and watery eyes.

Warnings:

- Do not use ifyou are taking a prescription monoamine oxidase inhibitor (MAOI) (certain drugs for depression, psychiatric, or emotional conditions, or Parkinson's disease), or for 2 weeks after stopping the MAOI drug. If you do not know if you are taking a prescription drug that contains an MAOI, ask your doctor or pharmacist before taking this product.

Ask a doctor before use if you aretaking sedatives or tranquilizers.

Ask a doctor before use if you have

- heart disease
- high blood pressure
- thyroid disese
- diabetes
- glucoma
- difficulty in urination due to the enlargement of the prostate gland.

When using this product

- do not exceed the recommended dosage
- excitability may occur, especially in children
- drowsiness may occur
- avoid alcoholic beverages
- alcohol, sedatives and tranquilizers may increase drowsiness
- use caution when driving a motor vehicle or operating machinery

Stop use and ask a doctor if

- nervousness, dizziness or sleeplessness occur
- symptoms do not improve within 7 days or occur with a fever.

KEEP OUT OF REACH OF CHILDREN

Keep out of the reach of children.In case of overdose, get medical help or contact a Poison Control Center right away.

PREGNANCY OR BREAST FEEDING

If pregnant or breast-feeding,ask a Health Professional before use.

DOSAGE AND ADMINISTRATION

Directions:Do not exceed more than 4 doses in any 24-hour period or as directed by a doctor.

Age | Dose
Adults and children 12 years of age and over | take two teaspoonfuls (10 mL) every 4 to 6 hours
Children 6 to under 12 years of age | take one teaspoonful (5 mL) every 4 to 6 hours
Children under 6 years of age | ask a doctor

Other Information:

- Store at controlled room temperature 20-25 degree celcius (68-77 degree farenheit); excursions permitted to 15-30 degree clecius (59-86 degree farenheit) (See USP Controlled Room Temperture) Tamper evident by imprinted heat seal under cap
- Do not use if there is evidence of tampering
- WARNING: Phenylketonuric: Contains 13.5 mg of Phenylalanine per 5 mL (one teaspoonful) dose.

INACTIVE INGREDIENT

Inactive Ingredients: citric acid, glycerine, menthol, methylparaben, propylene glycol, propylparaben, purified water, sodium citrate and sucralose

Questions or Comments? 1-866-595-5598